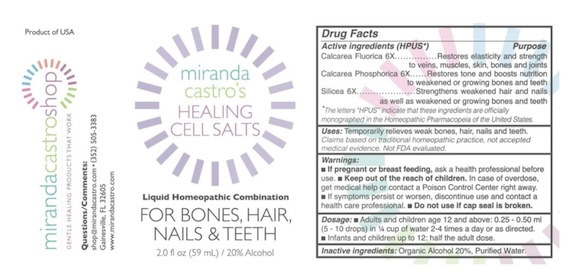 DRUG LABEL: Miranda Castros Healing Cell Salts
NDC: 82586-300 | Form: LIQUID
Manufacturer: MIRANDA CASTRO'S SHOP, LLC
Category: homeopathic | Type: HUMAN OTC DRUG LABEL
Date: 20251023

ACTIVE INGREDIENTS: CALCIUM FLUORIDE 6 [hp_X]/1 mL; SILICON DIOXIDE 6 [hp_X]/1 mL; TRIBASIC CALCIUM PHOSPHATE 6 [hp_X]/1 mL
INACTIVE INGREDIENTS: WATER; ALCOHOL

Miranda Castro's Healing Cell Salts - Liquid

Active Ingredients

Calcarea Fluorica 6X

Calcarea Phosphorica 6X

Silicea 6X

Uses

Temporarily relieves weak bones, hair, nails and teeth.

Dosage

Adults and children 12 and above: 0.25 to 0.5 ml (5-10 drops) in ¼ cup of water 2-4 times a day or as directed.

Infants and children up to 12: half the adult dose.

Inactive Ingredients: Organic alcohol 20%, Purified water

PURPOSE

Calcarea Fluorica - restores elasticity to veins, muscles, skin, bones and joints

Calcarea Phosphorica - Restores tone and boosts nutrition to weakened or growing bones and teeth

Silicea - Strengthens weakened hair and nails as well as weakened bones and teeth.

The letters HPUS indicate that these ingredients are officially monographed in the Homeopathic Pharmacopoeia of the United States.

Keep out of reach of children. In case of overdose, get medical help or contact a Poison Control Center right away.

Warnings

If symptoms persist or worsen, discontinue use and contact a healthcare professional.

Do not use if cap seal is broken.

Questions/Comments

shop@mirandacastro.com (352) 505-3383

If pregnant or breast-feeding, ask a health professional before use.